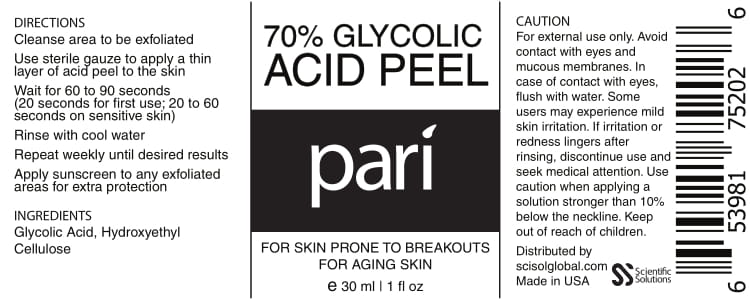 DRUG LABEL: Glycolic Acid
NDC: 71718-703 | Form: LIQUID
Manufacturer: Scientific Solutions Global LLC
Category: otc | Type: HUMAN OTC DRUG LABEL
Date: 20191003

ACTIVE INGREDIENTS: GLYCOLIC ACID 0.7 1/9 mL
INACTIVE INGREDIENTS: HYDROXYETHYL CELLULOSE (100 MPA.S AT 2%)

PACKAGE LABEL

INGREDIENTS

Glycolic Acid

PURPOSE

FOR SKIN PRONE TO BREAKOUTS
FOR AGING SKIN

Keep out of reach of children.

WARNINGS

CAUTION
For external use only. Avoid contact with eyes and\ mucous membranes. In case of contact with eyes, flush with water. Some users may experience mild skin irritation. If irritation or redness lingers after rinsing, discontinue use and seek medical attention. Use caution when applying a solution stronger than 10% below the neckline. Keep out of reach of children.

PURPOSE

FOR SKIN PRONE TO BREAKOUTS
FOR AGING SKIN

DIRECTIONS
Cleanse area to be exfoliated

Use sterile gauze to apply a thin layer of acid peel to the skin

Wait for 60 to 90 seconds (20 seconds for first use; 20 to 60 seconds on sensitive skin)

Rinse with cool water

Repeat weekly until desired results

Apply sunscreen to any exfoliated areas for extra protection

INACTIVE INGREDIENT

Hydroxyethyl Cellulose

DOSAGE AND ADMINISTRATION

Cleanse area to be exfoliated

Use sterile gauze to apply a thin layer of acid peel to the skin

Wait for 60 to 90 seconds (20 seconds for first use; 20 to 60 seconds on sensitive skin)

Rinse with cool water

Repeat weekly until desired results

Apply sunscreen to any exfoliated areas for extra protection

INDICATIONS AND USAGE

FOR SKIN PRONE TO BREAKOUTS
FOR AGING SKIN